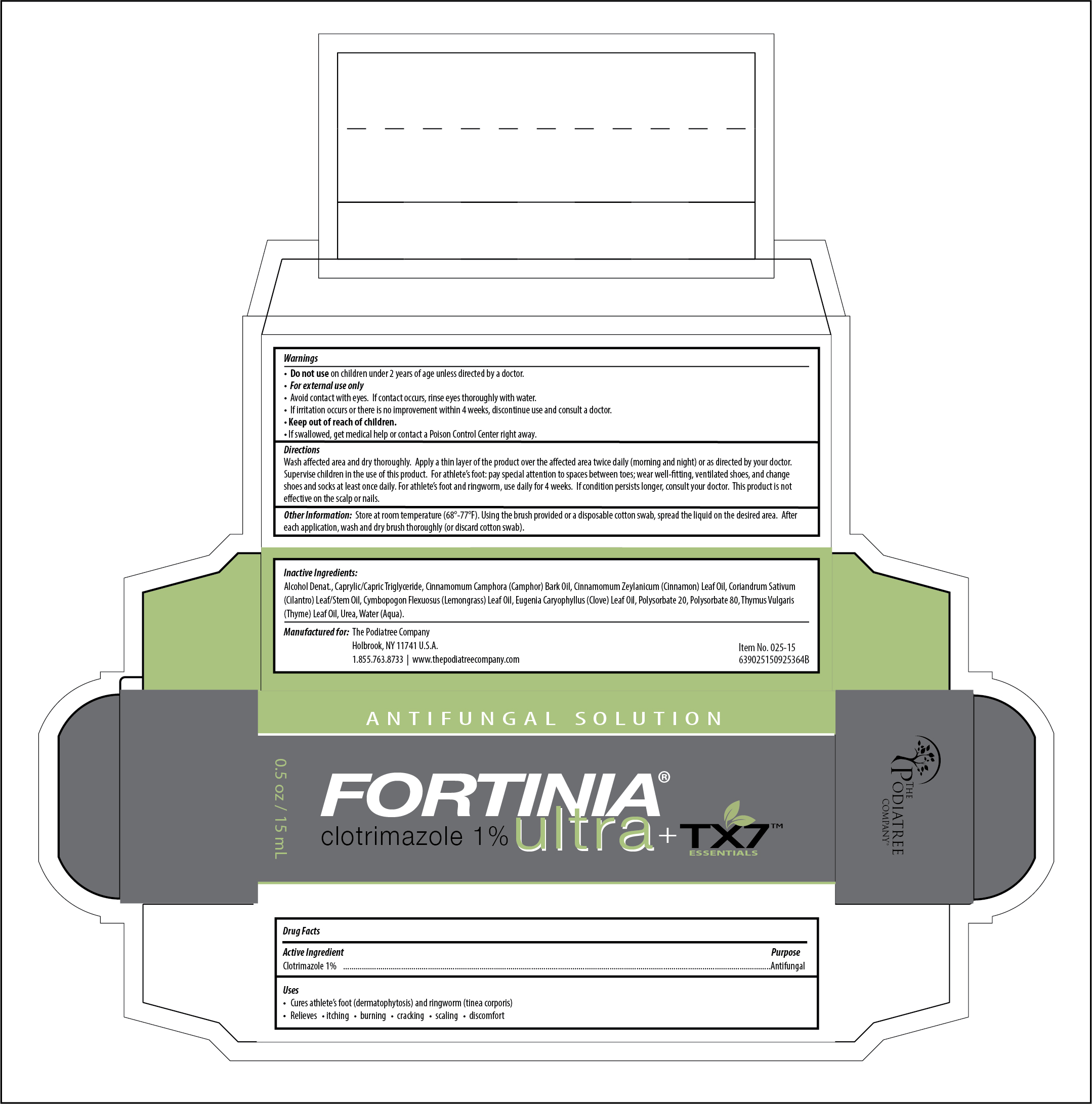 DRUG LABEL: Fortinia Ultra
NDC: 54633-025 | Form: SOLUTION
Manufacturer: The Podiatree Company
Category: otc | Type: HUMAN OTC DRUG LABEL
Date: 20251107

ACTIVE INGREDIENTS: CLOTRIMAZOLE 1 g/100 mL
INACTIVE INGREDIENTS: CYMBOPOGON FLEXUOSUS LEAF; THYMUS VULGARIS (THYME) FLOWER/LEAF OIL; EUGENIA CARYOPHYLLUS (CLOVE) LEAF OIL; POLYSORBATE 80; UREA; CAPRYLIC/CAPRIC TRIGLYCERIDE; CINNAMOMUM ZEYLANICUM LEAF OIL; POLYSORBATE 20; CINNAMOMUM CAMPHORA (CAMPHOR) BARK OIL; AQUA; ALCOHOL; CILANTRO

Fortinia Ultra Antifungal Solution

ACTIVE INGREDIENTS

Clotrimazole 1%

PURPOSE

Antifungal

USES

• Cures athlete’s foot (dermatophytosis) and ringworm (tinea corporis)
• Relieves • itching • burning • cracking • scaling • discomfort

DIRECTIONS

Wash affected area and dry thoroughly. Apply a thin layer of the product over the affected area twice daily (morning and night) or as directed by your doctor. Supervise children in the use of this product. For athlete’s foot: pay special attention to spaces between toes; wear well-fitting, ventilated shoes, and change shoes and socks at least once daily. For athlete’s foot and ringworm, use daily for 4 weeks. If condition persists longer, consult your doctor. This product is not effective on the scalp or nails.

WARNINGS

• Do not use on children under 2 years of age unless directed by a doctor.

• For external use only
• Avoid contact with eyes. If contact occurs, rinse eyes thoroughly with water.
• If irritation occurs or there is no improvement within 4 weeks, discontinue use and consult a doctor.
• If swallowed, get medical help or contact a Poison Control Center right away.

PRECAUTIONS

Keep out of reach of children.

OTHER INFORMATION

Store at room temperature (68°-77°F). Using the brush provided or a disposable cotton swab, spread the liquid on the desired area. After each application, wash and dry brush thoroughly (or discard cotton swab).

INACTIVE INGREDIENTS

Alcohol Denat., Caprylic/Capric Triglyceride, Cinnamomum Camphora (Camphor) Bark Oil, Cinnamomum Zeylanicum (Cinnamon) Leaf Oil, Coriandrum Sativum (Cilantro) Leaf/Stem Oil, Cymbopogon Flexuosus (Lemongrass) Leaf Oil, Eugenia Caryophyllus (Clove) Leaf Oil, Polysorbate 20, Polysorbate 80, Thymus Vulgaris (Thyme) Leaf Oil, Urea, Water (Aqua)